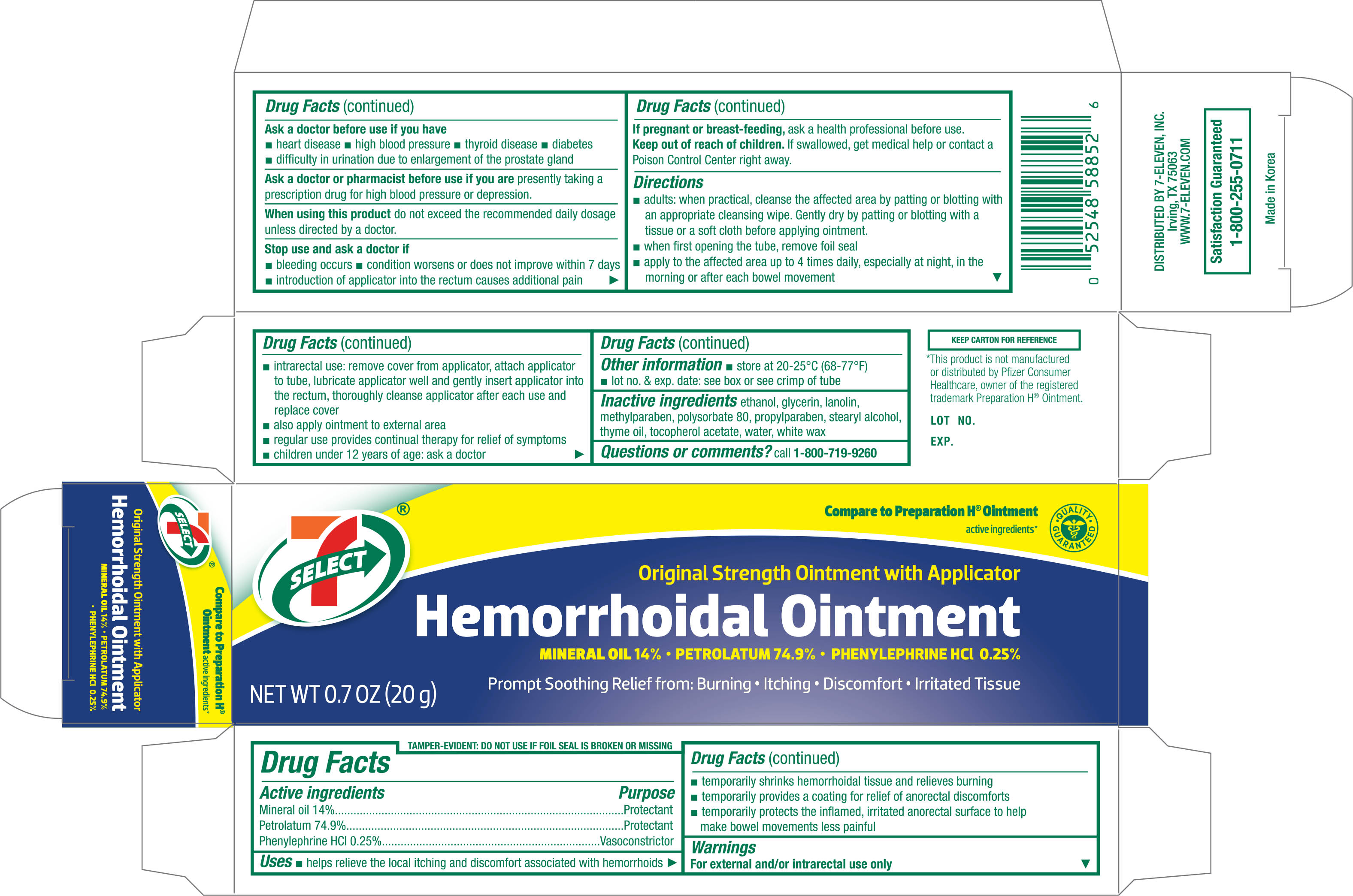 DRUG LABEL: 7 Select Hemorrhoidal Original Strength
NDC: 10202-526 | Form: OINTMENT
Manufacturer: 7-ELEVEN, INC.
Category: otc | Type: HUMAN OTC DRUG LABEL
Date: 20161207

ACTIVE INGREDIENTS: PHENYLEPHRINE HYDROCHLORIDE 2.5 mg/1 g; MINERAL OIL 140 mg/1 g; PETROLATUM 749 mg/1 g
INACTIVE INGREDIENTS: ALCOHOL; GLYCERIN; LANOLIN; METHYLPARABEN; POLYSORBATE 80; PROPYLPARABEN; STEARYL ALCOHOL; THYME OIL; .ALPHA.-TOCOPHEROL ACETATE; WATER; WHITE WAX

Active ingredients Purpose

Mineral oil 14%......................................................Protectant

Petrolatum 74.9%..................................................Protectant

Phenylephrine HCl 0.25%.......................................Vasoconstrictor

Uses

- helps relieve the local itching and discomfort associated with hemorrhoids
- temporarily shrinks hemorrhoidal tissue and relieves burning
- temporarily provides a coating for relief of anorectal discomforts
- temporarily protects the inflamed, irritated anorectal surface to help make bowel movements less painful

Warnings

For external and/or intrarectal use only

Ask a doctor before use if you have

- heart disease
- high blood pressure
- thyroid disease
- diabetes
- difficulty in urination due to enlargement of the prostate gland

Ask a doctor or pharmacist before use if you are presently taking a prescription drug for high blood pressure or depression.

When using this product do not exceed the recommended daily dosage unless directed by a doctor.

Stop use and ask a doctor if

- bleeding occurs
- condition worsens or does not improve within 7 days
- introduction of applicator into the rectum causes additional pain

PREGNANCY OR BREAST FEEDING

If pregnant or breast-feeding, ask a health professional before use.

Keep out of reach of children. If swallowed, get medical help or contact a Poison Control Center right away.

Directions

- adults: when practical, cleanse the affected area by patting or blotting with an appropriate cleansing wipe. Gently dry by patting or blotting with a tissue or a soft cloth before applying ointment.
- when first opening the tube, remove foil seal
- apply to the affected area up to 4 times daily, especially at night, in the morning or after each bowel movement

Other information

- store at 20-25°C (68-77°F)
- lot no. & exp. date: see box or see crimp of tube

Inactive ingredients

ethanol, glycerin, lanolin, methylparaben, polysorbate 80, propylparaben, stearyl alcohol, thyme oil, tocopherol acetate, water, white wax

DOSAGE AND ADMINISTRATION

DISTRIBUTED BY 7-ELEVEN, INC.

Irving, TX 75063

WWW.7-ELEVEN.COM

Made in Korea